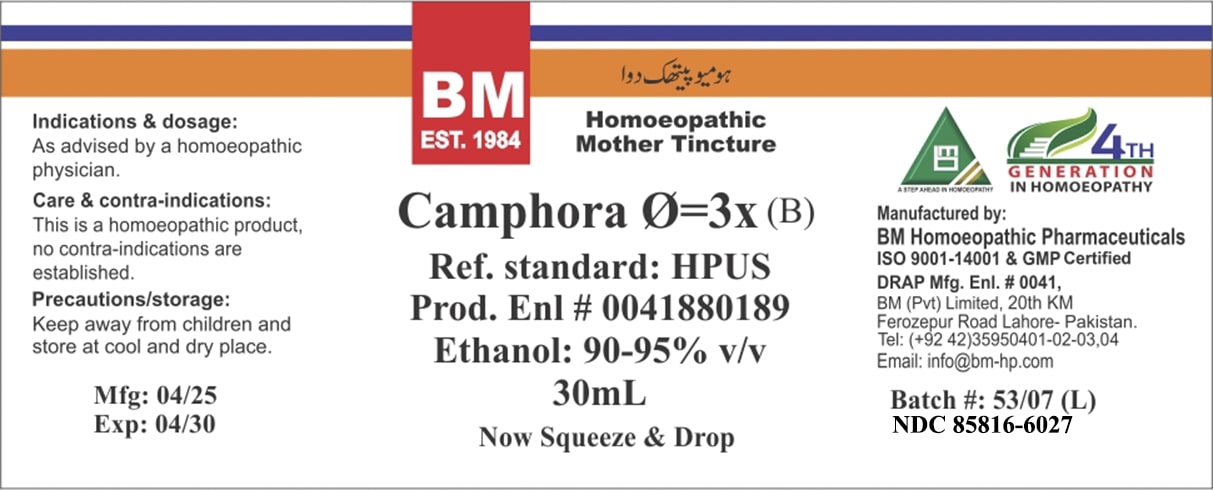 DRUG LABEL: BM Camphora
NDC: 85816-6027 | Form: TINCTURE
Manufacturer: BM Private Limited
Category: homeopathic | Type: HUMAN OTC DRUG LABEL
Date: 20250627

ACTIVE INGREDIENTS: CAMPHOR (NATURAL) 1 [hp_X]/1 mL
INACTIVE INGREDIENTS: ALCOHOL 0.95 mL/1 mL

BM Camphora tincture

ACTIVE INGREDIENT

Camphora

INACTIVE INGREDIENT

alcohol

PURPOSE

Indications & dosage: As advised by a homoeopathic physician.

Indications & dosage: As advised by a homoeopathic physician.

Indications & dosage: As advised by a homoeopathic physician.

CONTRAINDICATIONS

Care & contra-indications: This is a homoeopathic product, no contra-indications are established.

KEEP OUT OF REACH OF CHILDREN

Precautions/storage: Keep away from children and store at cool and dry place.

WARNINGS

Precautions/storage: Keep away from children and store at cool and dry place.

STORAGE AND HANDLING

Precautions/storage: Keep away from children and store at cool and dry place.

Entire package label